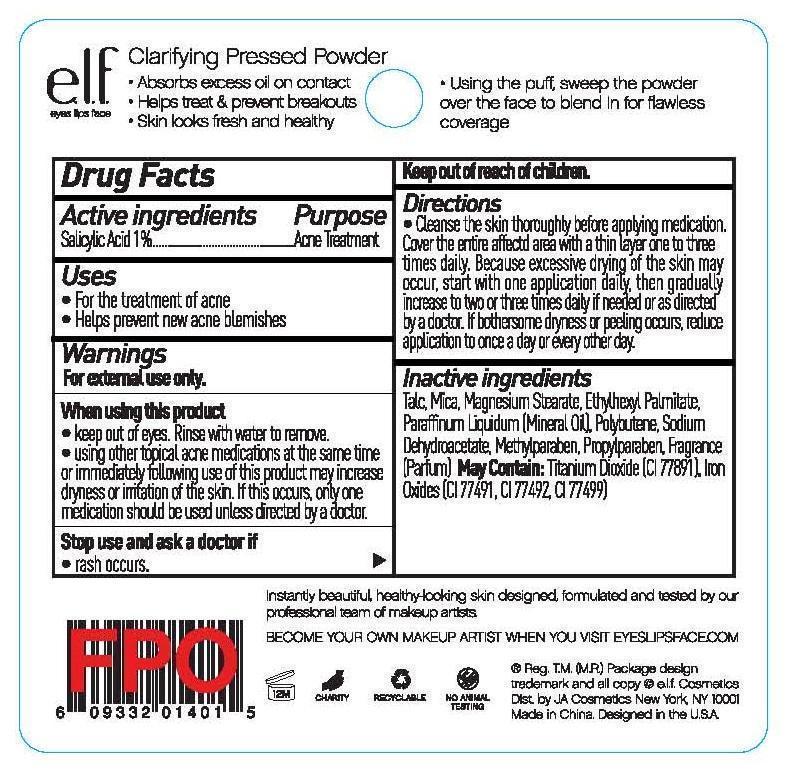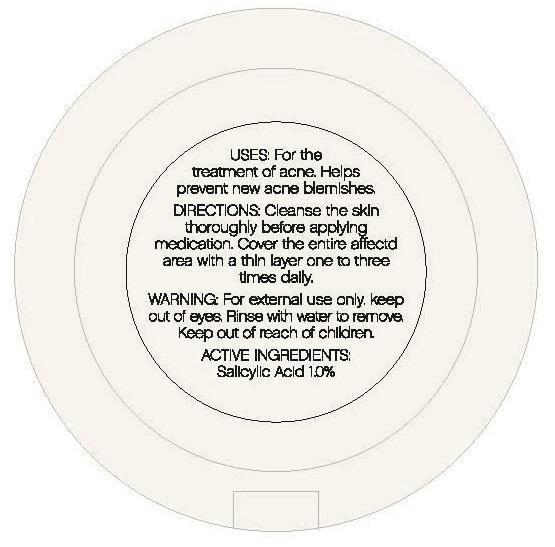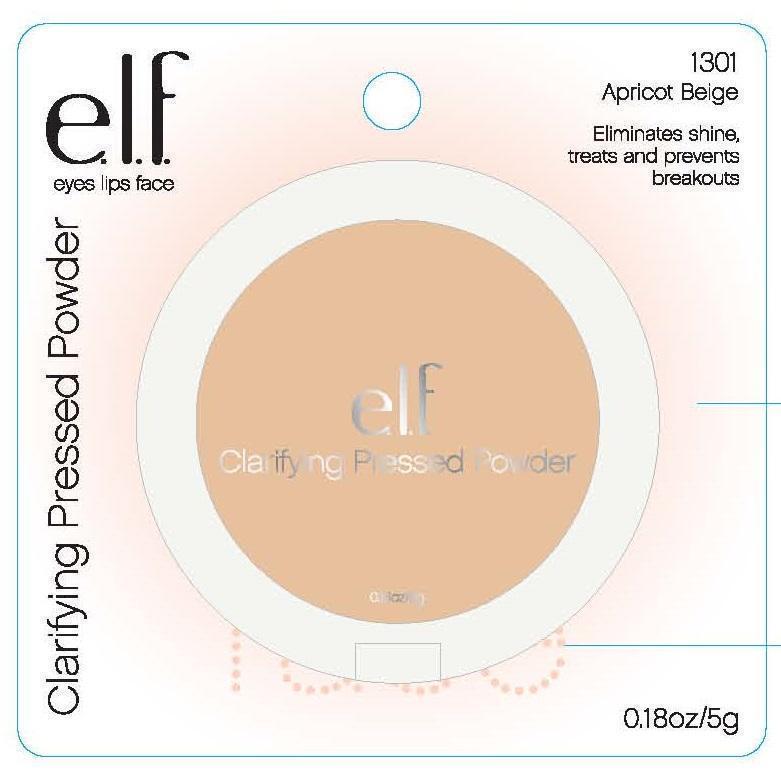 DRUG LABEL: CLARIFYING PRESSED POWDER
NDC: 76354-201 | Form: POWDER
Manufacturer: J. A. Cosmetics U.S. INC
Category: otc | Type: HUMAN OTC DRUG LABEL
Date: 20140319

ACTIVE INGREDIENTS: SALICYLIC ACID 1 g/100 g
INACTIVE INGREDIENTS: TALC; MICA; MAGNESIUM STEARATE; ETHYLHEXYL PALMITATE; MINERAL OIL; POLYBUTENE (1400 MW); SODIUM DEHYDROACETATE; METHYLPARABEN; PROPYLPARABEN; TITANIUM DIOXIDE; FERRIC OXIDE RED; FERRIC OXIDE YELLOW; FERROSOFERRIC OXIDE

Active Ingredient:

SALICYLC ACID 1%

Purpose:

ACNE TRATMENT

Uses:

- FOR THE TREATMENT OF ACNE
- HELPS PREVENT NEW ACNE BLEMISHES

Warning:

For external use only

When Using This Product

- KEEP OUT OF EYES. RINSE WITH WATER TO REMOVE.
- USING OTHER TOPICAL ACNE MEDICATIONS AT THE SAME TIME OR IMMEDIATELY FOLLOWING USE OF THIS PRODUCT MAY INCREASE DRYNESS OR IRRITATION OF SKIN. IF THIS OCCURS, ONLY ONE MEDICATION SHOULD BE USED UNLESS DIRECTED BY A DOCTOR.

Stop use and ask a doctor if

- rash occurs.

KEEP OUT OF REACH OF CHILDREN.

Directions:

- CLEANSETHE SKIN THOROUGHLY BEFORE APPLYING MEDICTION.
  COVER THE ENTIRE AFFECTED AREA WITH A THIN LAYER ONE TO THREE TIMES DAILY. BEACAUSE EXCESSIVE DRYING OF SKIN MAY OCCUR, START WITH ONE APPLICATION DAILY, THEN GRADUALLY INCREASE TO TWO OR THREE TIMES DAILY IF NEEDED OR AS DIRECTED BY A DOCTOR. IF BOTHERSOME DRYNESS OR PEELING OCCURS, REDUCE APPLICATION TO ONCE A DAY OR EVERY OTHER DAY.

Inactive Ingredient:

TALC, MICA, MAGNESIUM STEARATE, ETHYLHEXYL PALMITATE, PARAFFINUM LIQUIDUM (MINERAL OIL), POLYBUTENE, SODIUM DEHYDROACETATE, METHYLPARABEN, PROPYLPARABEN, FRAGRANCE (PARFUM)

May Contain: TITANUM DIOXIDE (CI 77891), Iron Oxides (CI 77491, CI 77492, CI 77499)